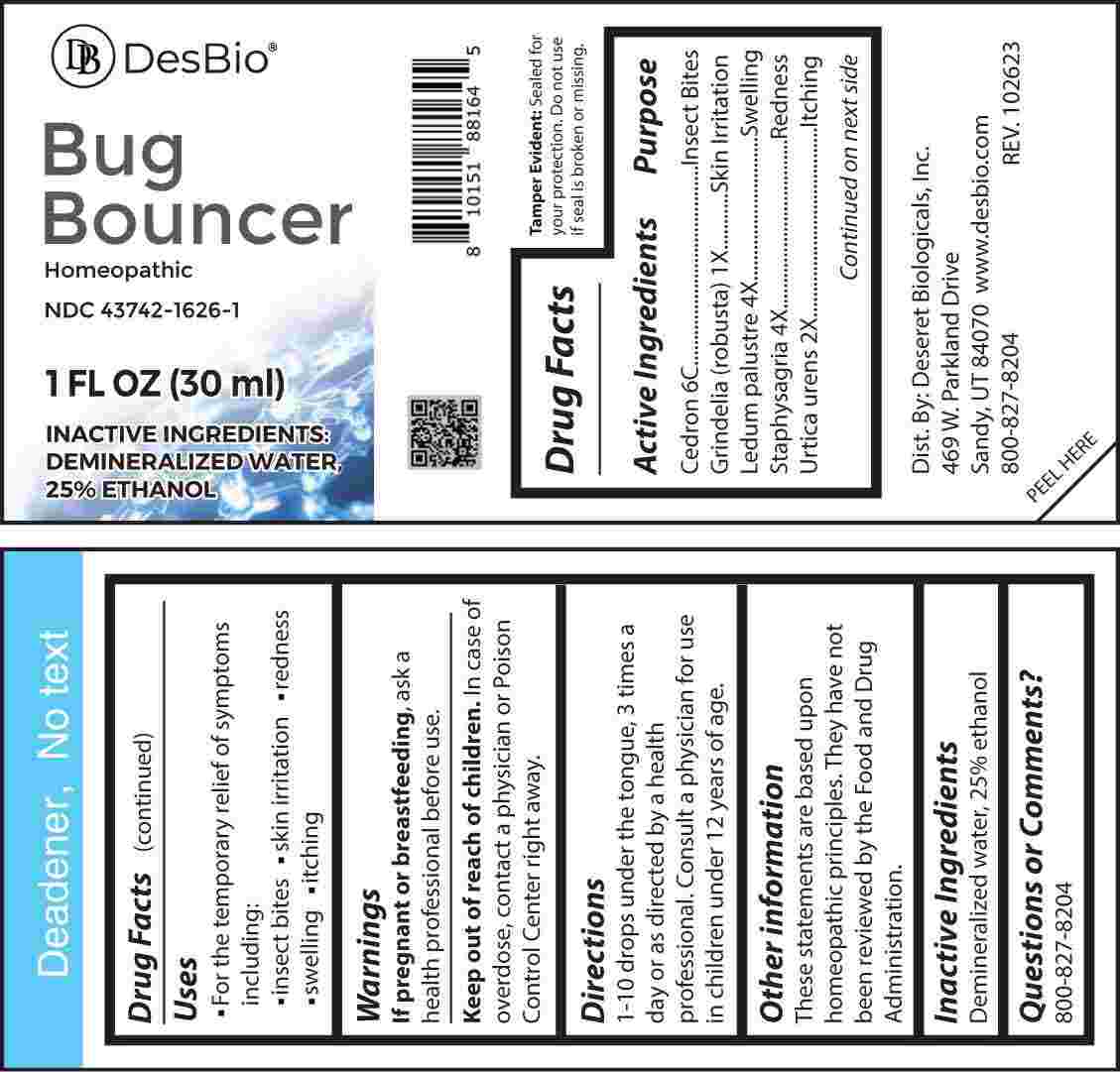 DRUG LABEL: Bug Bouncer
NDC: 43742-1626 | Form: LIQUID
Manufacturer: Deseret Biologicals, Inc.
Category: homeopathic | Type: HUMAN OTC DRUG LABEL
Date: 20240220

ACTIVE INGREDIENTS: GRINDELIA HIRSUTULA WHOLE 1 [hp_X]/1 mL; URTICA URENS WHOLE 2 [hp_X]/1 mL; LEDUM PALUSTRE TWIG 4 [hp_X]/1 mL; DELPHINIUM STAPHISAGRIA SEED 4 [hp_X]/1 mL; SIMABA CEDRON SEED 6 [hp_C]/1 mL
INACTIVE INGREDIENTS: WATER; ALCOHOL

DRUG FACTS:

ACTIVE INGREDIENTS:

Cedron 6C, Grindelia (Robusta) 1X, Ledum Palustre 4X, Staphysagria 4X, Urtica Urens 2X.

PURPOSE:

Cedron – Insect Bites, Grindelia (Robusta) – Skin Irritation, Ledum Palustre - Swelling, Staphysagria - Redness, Urtica Urens - Itching.

USES:

• For the temporary relief of symptoms including:

• insect bites • skin irritation • redness

• swelling • itching

These statements are based upon homeopathic principles. They have not been reviewed by the Food and Drug Administration.

WARNINGS:

If pregnant or breast-feeding, ask a health professional before use.

Keep out of reach of children. In case of overdose, contact a physician or Poison Control Center right away.

Tamper Evident: Sealed for your protection. Do not use if seal is broken or missing.

KEEP OUT OF REACH OF CHILDREN.

In case of overdose, contact a physician or Poison Control Center right away.

DIRECTIONS:

1-10 drops under the tongue, 3 times a day or as directed by a health professional. Consult a physician for use in children under 12 years of age.

INACTIVE INGREDIENTS:

Demineralized water, 25% ethanol

QUESTIONS:

Dist. By: Deseret Biologicals, Inc.

469 W. Parkland Drive

Sandy, UT 8407

www.desbio.com

800-827-8204

PACKAGE LABEL DISPLAY:

DesBio

Bug Bouncer

Homeopathic

NDC 43742-1626-1

1 FL OZ (30 ml)